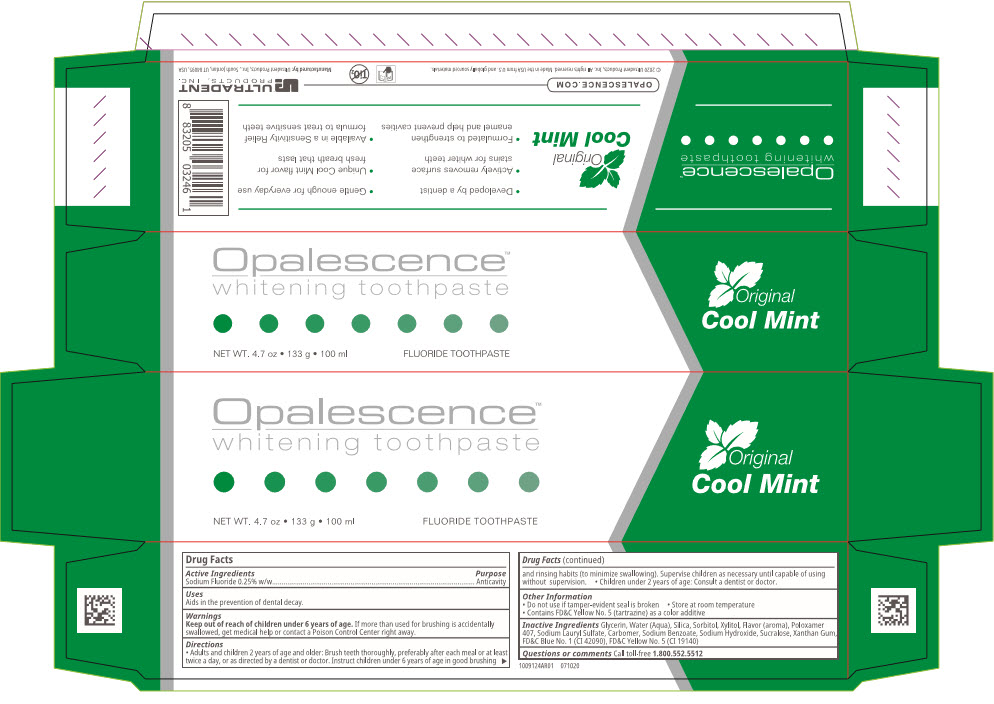 DRUG LABEL: Opalescence Whitening
NDC: 51206-302 | Form: GEL, DENTIFRICE
Manufacturer: Ultradent Products, Inc
Category: otc | Type: HUMAN OTC DRUG LABEL
Date: 20251117

ACTIVE INGREDIENTS: SODIUM FLUORIDE 1.1 mg/1 g
INACTIVE INGREDIENTS: GLYCERIN; SACCHARIN SODIUM; FD&C BLUE NO. 1; FD&C YELLOW NO. 5; XANTHAN GUM; SODIUM LAURYL SULFATE; WATER; SORBITOL; SODIUM BENZOATE; XYLITOL; SILICON DIOXIDE; METHYL SALICYLATE

Opalescence™
whitening toothpaste

Drug Facts

Active Ingredients

Sodium Fluoride 0.25% w/w

Purpose

Anticavity

Uses

Aids in the prevention of dental decay.

Warnings

Keep out of reach of children under 6 years of age.If more than used for brushing is accidentally swallowed, get medical help or contact a Poison Control Center right away.

Directions

- Adults and children 2 years of age and older: Brush teeth thoroughly, preferably after each meal or at least twice a day, or as directed by a dentist or doctor. Instruct children under 6 years of age in good brushing and rinsing habits (to minimize swallowing). Supervise children as necessary until capable of using without supervision.
- Children under 2 years of age: Consult a dentist or doctor.

Other Information

- Do not use if tamper-evident seal is broken
- Store at room temperature
- Contains FD&C Yellow No. 5 (tartrazine) as a color additive

Inactive Ingredients

Glycerin, Water (Aqua), Silica, Sorbitol, Xylitol, Flavor (aroma), Poloxamer 407, Sodium Lauryl Sulfate, Carbomer, Sodium Benzoate, Sodium Hydroxide, Sucralose, Xanthan Gum, FD&C Blue No. 1 (CI 42090), FD&C Yellow No. 5 (CI 19140)

Questions or comments

Call toll-free 1.800.552.5512

Manufactured by:Ultradent Products, Inc., South Jordan, UT 84095, USA

PRINCIPAL DISPLAY PANEL - 100 ml Tube Box

Opalescence™
whitening toothpaste

NET WT. 4.7 oz • 133 g • 100 ml
FLUORIDE TOOTHPASTE

Original
Cool Mint